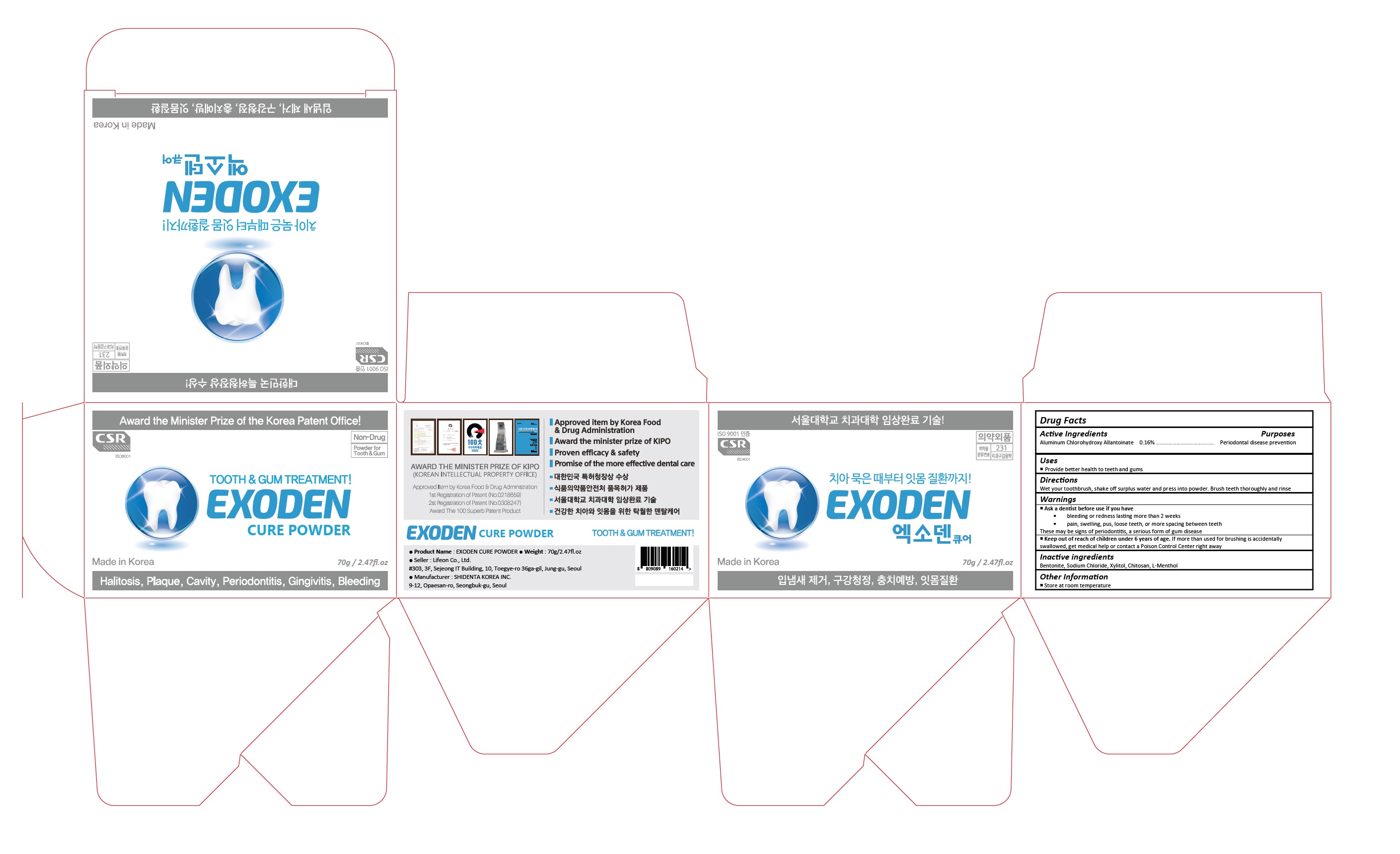 DRUG LABEL: Exoden Cure Powder
NDC: 70602-004 | Form: POWDER
Manufacturer: LIFEON Corp.
Category: otc | Type: HUMAN OTC DRUG LABEL
Date: 20220309

ACTIVE INGREDIENTS: ALCLOXA 0.16 g/100 g
INACTIVE INGREDIENTS: BENTONITE; SODIUM CHLORIDE; XYLITOL; LEVOMENTHOL

70602-004_Exoden Cure Powder

ACTIVE INGREDIENT

Aluminum Chlorohydroxy Allantoinate 0.16%

PURPOSE

Oral Health Care

INDICATIONS AND USAGE

Provide better health to teeth and gums

DOSAGE AND ADMINISTRATION

Wet your toothbrush, shake off surplus water and press into powder. Brush teeth thoroughly and rinse

WARNINGS

Ask a dentist before use if you have
• bleeding or redness lasting more than 2 weeks
• pain, swelling, pus, loose teeth, or more spacing between teeth
These may be signs of periodontitis, a serious form of gum disease

Keep out of reach of children under 6 years of age. If more than used for brushing is accidentally swallowed, get medical help or contact a Poison Control Center right away

INACTIVE INGREDIENT

Bentonite, Sodium Chloride, Xylitol, Chitosan, L-Menthol